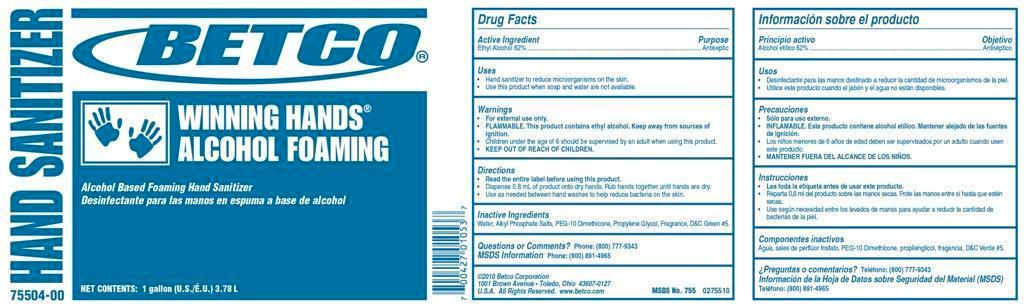 DRUG LABEL: Winning Hands Alcohol Foaming
NDC: 65601-755 | Form: SOAP
Manufacturer: Betco Corporation, Ltd.
Category: otc | Type: HUMAN OTC DRUG LABEL
Date: 20121112

ACTIVE INGREDIENTS: ALCOHOL 0.7 mL/1 mL
INACTIVE INGREDIENTS: WATER; DIETHANOLAMINE; PEG-10 DIMETHICONE (600 CST); PROPYLENE GLYCOL; D&C GREEN NO. 5

Winning Hands Alcohol Foaming

Winning Hands Alcohol Foaming

Active Ingredient

Ethyl Alcohol 62%

Winning Hands Alcohol Foaming

Uses

- Use hand sanitizer to reduce microorganisms on the skin.
- Use this product when soap and water are not available.

Winning Hands Alcohol Foaming

Warnings

- For external use only.
- FLAMMABLE. This product contains ethyl alcohol. Keep away from sources of ignition.
- Children under the age of 6 should be supervised by an adult when using this product.
- Discontinue use is irritation or redness develops.
- KEEP OUT OF REACH OF CHILDREN.

Winning Hands Alcohol Foaming

Directions

- Read the entire label before using this product.
- Dispense 0.8 mL of product onto dry hands. Rub hands together until hands are dry.
- Use as needed between hand washes to help reduce bacteria on the skin.

Winning Hands Alcohol Foaming

Inactive Ingredients

Water, Alkyl Phosphate Salts, PEG-10 Dimethicone, Propylene Glycol, Fragrance, D&C Green #5.

Winning Hands Alcohol Foaming

Questions or Comments? Phone: (800) 777-9343

MDS information:(800) 891-4965

Winning Hands Alcohol Foaming

Purpose

Antiseptic

Winning Hands Alcohol Foaming

KEEP OUT OF REACH OF CHILDREN

Winning Hands Alcohol Foaming

75504-00 HAND SANITIZER

Alcohol Based Foaming Hand Sanitizer

Net Contents: 1 gallon (U.S./E.U.) 3.78 L